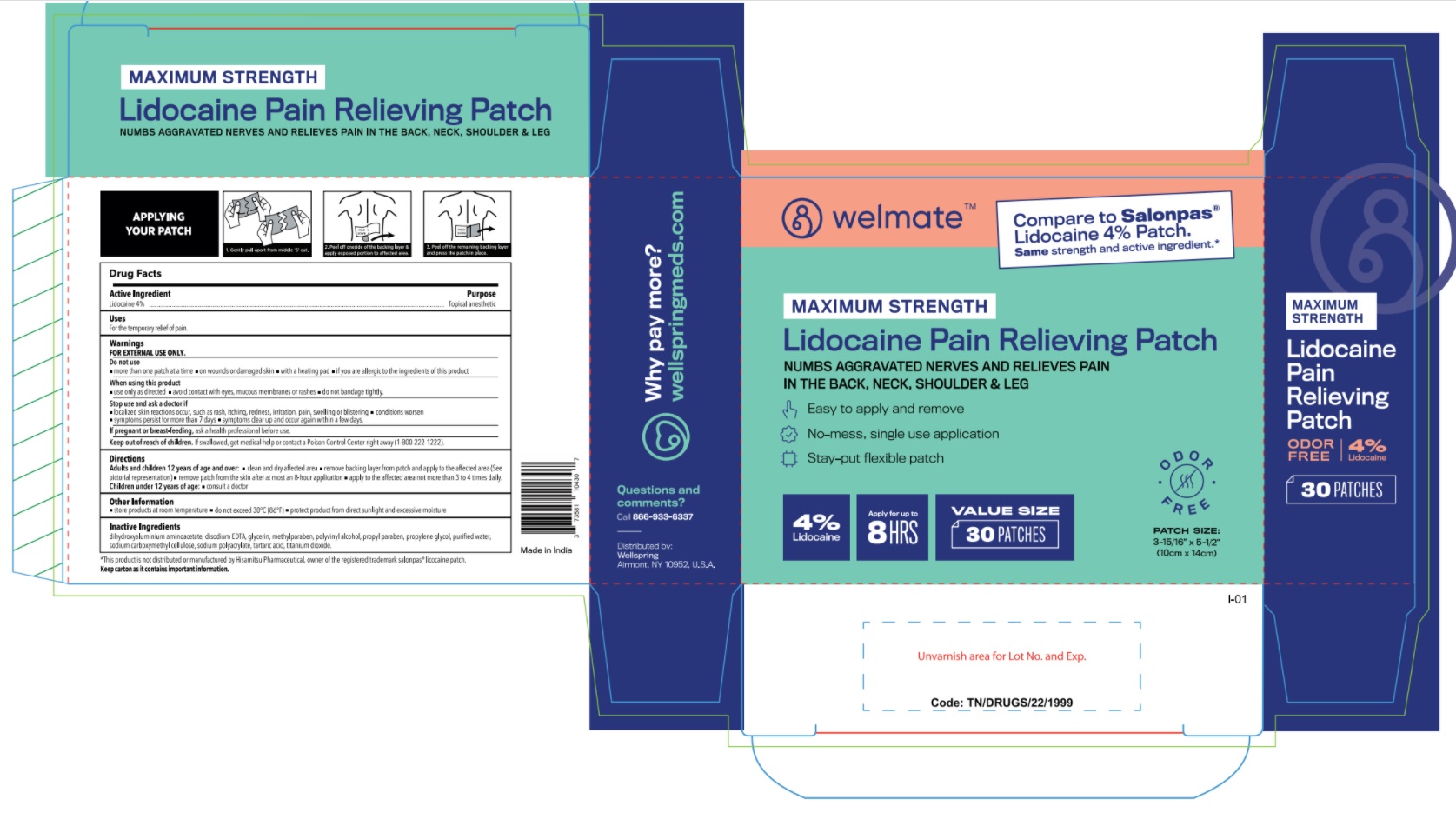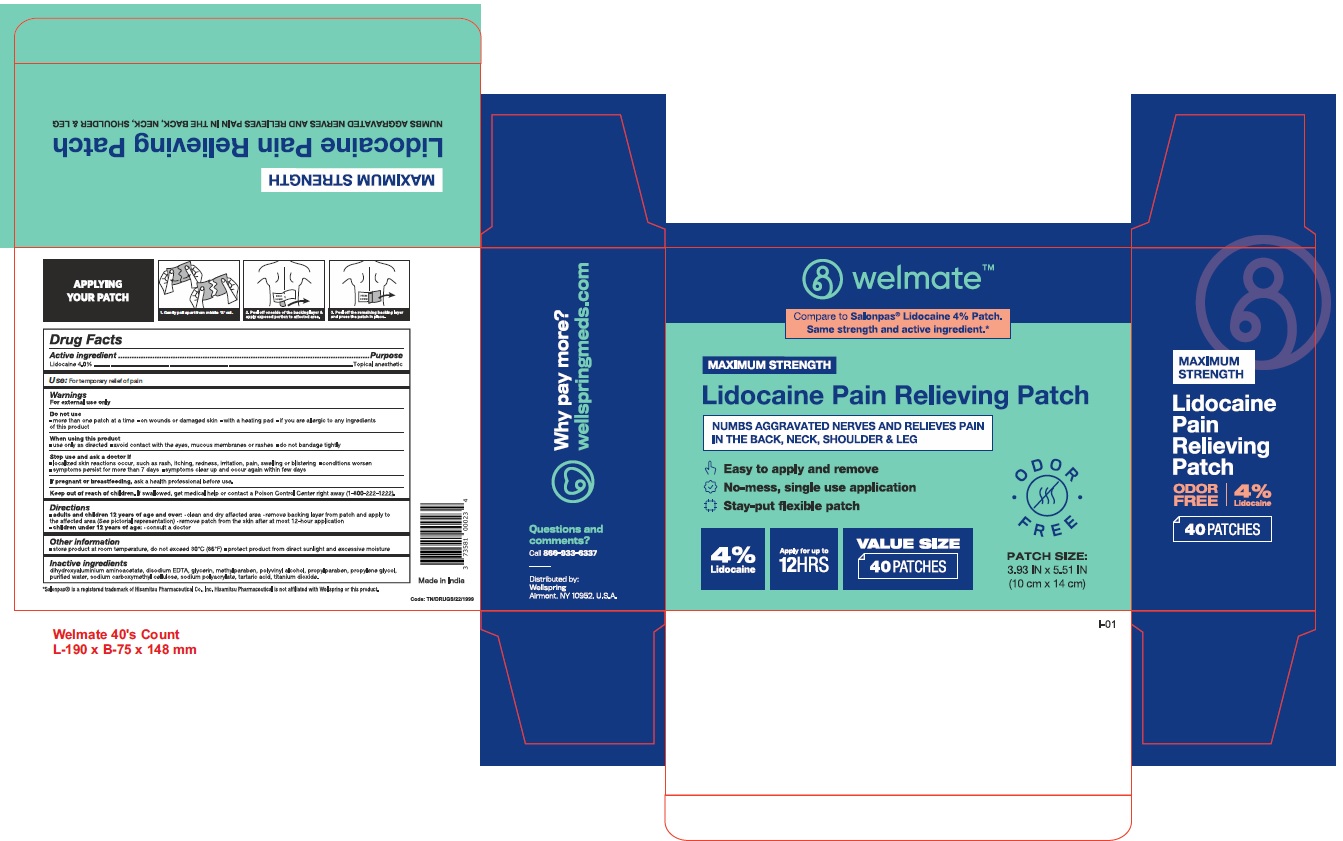 DRUG LABEL: Pain Relieving Lidocaine Patch
NDC: 73581-001 | Form: PATCH
Manufacturer: YYBA CORP
Category: otc | Type: HUMAN OTC DRUG LABEL
Date: 20260114

ACTIVE INGREDIENTS: LIDOCAINE 40 mg/1 1
INACTIVE INGREDIENTS: TARTARIC ACID; WATER; CARBOXYMETHYLCELLULOSE SODIUM; DIHYDROXYALUMINUM AMINOACETATE; EDETATE DISODIUM ANHYDROUS; GLYCERIN; POLYVINYL ALCOHOL, UNSPECIFIED; METHYLPARABEN; PROPYLPARABEN; PROPYLENE GLYCOL; SODIUM POLYACRYLATE (8000 MW); TITANIUM DIOXIDE; SODIUM BORATE

YYBA - Welmate Lidocaine Pain Relieving Patch (73581-001)

Active ingredient

Lidocaine 4%

Purpose

Topical Anesthetic

Uses

Temporarily relieves minor pain

Warnings

For external use only

Do Not Use

- more than 1 patch on your body at a time or on cut, irritated or swollen skin
- on puncture wounds or damaged skin
- with a heating pad
- if you are allergic to ingredients of this product

When Using This Product

- use only as directed. Read and follow all directions and warnings on this label.
- do not allow contact with the eyes
- do not bandage tightly or apply local heat (such as heating pads) to the area of use
- do not use at the same time as other topical analgesics
- dispose of used patch in manner that always keeps product away from children or pets. Used patches still contain the drug product that can produce serious adverse effects if a child or pet chews or ingests this patch.

Stop Use and Ask a Doctor if

- condition worsens
- redness is present
- irritation develops
- symptoms persist for more than 7 days or clear up and occur again within a few days
- you experience signs of skin injury, such as pain, swelling, or blistering where the product was applied
- symptoms clear up and occur again within few days

If Pregnant or Breast Feeding

ask a health professional before use.

Keep Out of Reach of Children and Pets

If swallowed, get medical help or contact a Poison Control Center right away.

Directions

Adults and children over 12 years:

- clean and dry affected area
- remove backing from patch by firmly grasping both ends and gently pulling until backing separates in middle
- carefully remove from the skin after at most 8-hour application
- apply to the affected area not more than 3 to 4 times daily

children 12 years or younger:ask a doctor

Inactive Ingredients

dihydroxyaluminium aminoacetate, disodium EDTA, glycerin, methylparaben, polyvinyl alcohol, propyl paraben, propylene glycol, purified water, sodium carboxymethyl cellulose, sodium polyacrylate, tartaric acid, titanium oxide